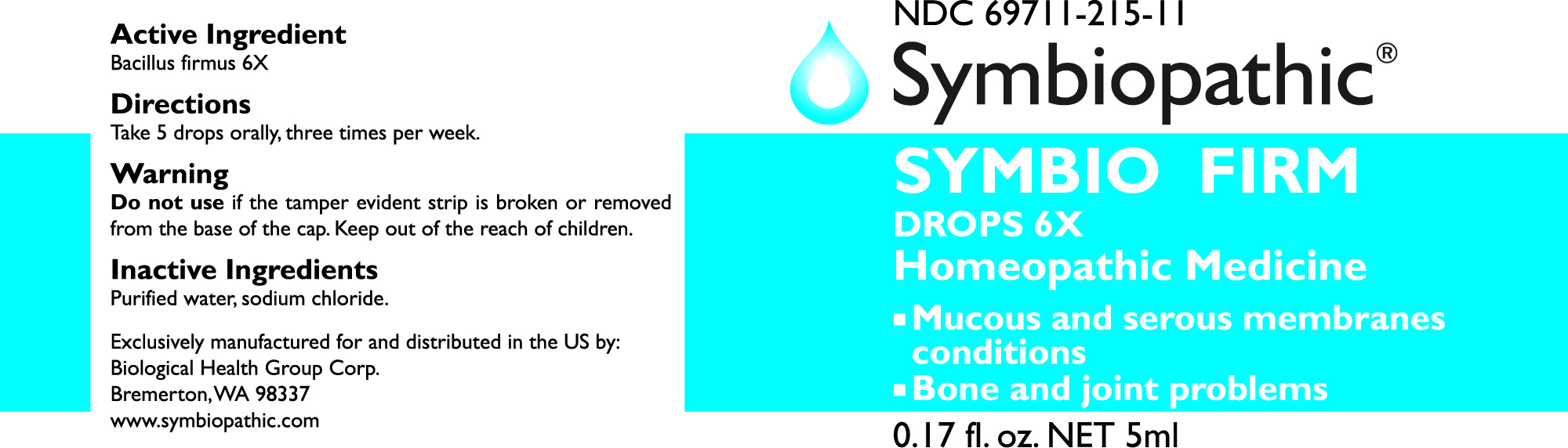 DRUG LABEL: SYMBIO FIRM DROPS
NDC: 69710-215 | Form: LIQUID
Manufacturer: Symbiopathic
Category: homeopathic | Type: HUMAN OTC DRUG LABEL
Date: 20251011

ACTIVE INGREDIENTS: BACILLUS FIRMUS 6 [hp_X]/1 mL
INACTIVE INGREDIENTS: SODIUM CHLORIDE; WATER

Firm 6X

ACTIVE INGREDIENTS:

Bacillus firmus 6X

WARNINGS:

Do not useif the tamper evident strip is broken or removed from the base of the cap.

DIRECTIONS:

Take 5 drops orally, three times per week.

INACTIVE INGREDIENTS:

Purified water USP, sodium chloride

KEEP OUT OF REACH OF CHILDREN:In case of overdose, get medical help or call a Poison Control Center right away.

INDICATIONS:

This remedy is indicated for symptoms associated with inflammation of serous and mucous membranes, bone infections and joint problems according to traditional homeopathic practice.*

QUESTIONS:

Call toll-free from US & CA +1-844-880-4881 or visit our website
www.biological-health.com

PURPOSE:

For internal indications according to traditional homeopathic practice.

If pregnant or breast feeding, ask a health professional before use.

ASK DOCTOR:

Consult a physician if symptoms worsen or last for more than 7 days.

OTHER INFORMATION:

Protect from light and heat.

For professional distribution only.

*These statements are based upon traditional homeopathic practice. They have not been reviewed by the Food and Drug Administration.